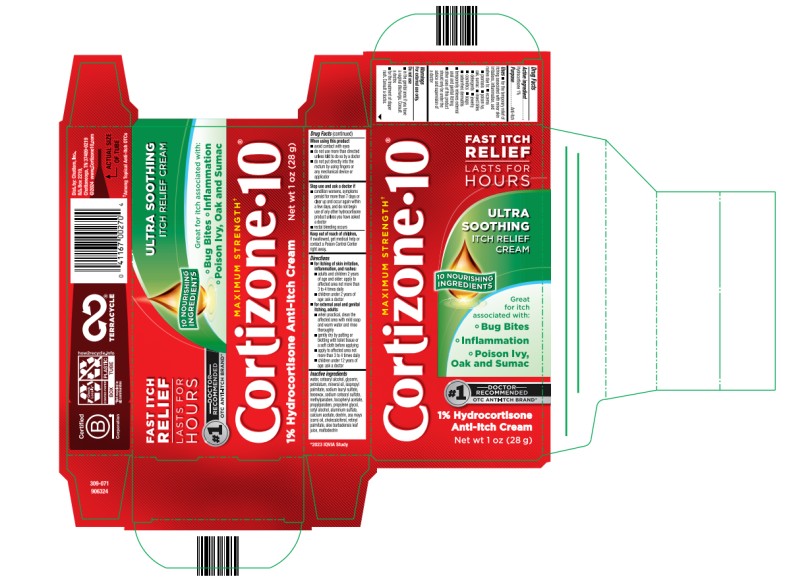 DRUG LABEL: Cortizone 10 Ultra Soothing Itch Relief
NDC: 41167-0029 | Form: CREAM
Manufacturer: Chattem, Inc.
Category: otc | Type: HUMAN OTC DRUG LABEL
Date: 20250221

ACTIVE INGREDIENTS: HYDROCORTISONE 1 g/100 g
INACTIVE INGREDIENTS: WATER; CETEARYL ALCOHOL; GLYCERIN; PETROLATUM; MINERAL OIL; ISOPROPYL PALMITATE; SODIUM LAURYL SULFATE; BEESWAX; SODIUM CETEARYL SULFATE; METHYLPARABEN; ALPHA-TOCOPHEROL ACETATE; PROPYLPARABEN; PROPYLENE GLYCOL; CETYL ALCOHOL; ALUMINUM SULFATE; CALCIUM ACETATE; DEXTRIN, POTATO; ZEA MAYS (CORN) OIL; CHOLECALCIFEROL; RETINYL PALMITATE; ALOE VERA LEAF; MALTODEXTRIN

Cortizone 10 Ultra Soothing Itch Relief Cream

Cortizone 10 Ultra Soothing Itch Relief Cream

Drug Facts

Active ingredients

Hydrocortisone 1%

Purpose

Anti-Itch

Uses

■ for the temporary relief of itching associated with minor skin irritations, inflammation, and rashes due to:
■ eczema ■ psoriasis ■ poison ivy, oak, sumac ■ insect bites ■ detergents ■ jewelry ■ cosmetics
■ soaps ■ seborrheic dermatitis

■ temporarily relieves external anal and genital itching

■ other uses of this product should be only under the advice and supervision of a doctor

Warnings

For external use only.

Do not use

■ in the genital area if you have a vaginal discharge. Consult a doctor. ■ for the treatment of diaper rash. Consult a doctor.

When using this product

■ avoid contact with eyes ■ do not use more than directed unless told to do so by a doctor ■ do not put directly into the rectum by using fingers or any mechanical device or applicator

Stop use and ask a doctor if

■ condition worsens, symptoms persist for more than 7 days or clear up and occur again within a few days, and do not begin use of any other hydrocortisone product unless you have asked a doctor

■ rectal bleeding occurs

Keep out of reach of children.

If swallowed, get medical help or contact a Poison Control Center right away.

Directions

■ for itching of skin irritation, inflammation, and rashes:
■ adults and children 2 years of age and older: apply to affected area not more than 3 to 4 times daily
■ children under 2 years of age: ask a doctor

■ for external anal and genital itching, adults

■ when practical, clean the affected area with mild soap and warm water and rinse thoroughly
■ gently dry by patting or blotting with toilet tissue or a soft cloth before applying
■ apply to affected area not more than 3 to 4 times daily
■ children under 12 years of age: ask a doctor

Inactive ingredients

water, cetearyl alcohol, glycerin, petrolatum, mineral oil, isopropyl palmitate, sodium lauryl sulfate, beeswax, sodium cetearyl sulfate, methylparaben, tocopheryl acetate, propylparaben, propylene glycol, cetyl alcohol, aluminum sulfate, calcium acetate, dextrin, zea mays (corn) oil, cholecalciferol, retinyl palmitate, aloe barbadensis leaf juice, maltodextrin

Principal Display Panel

MAXIMUM STRENGTH
Cortizone 10
ULTRA SOOTHING
ITCH RELIEF
CREAM
1% Hydrocortisone
Anti-Itch Cream
Net wt 1 oz (28 g)